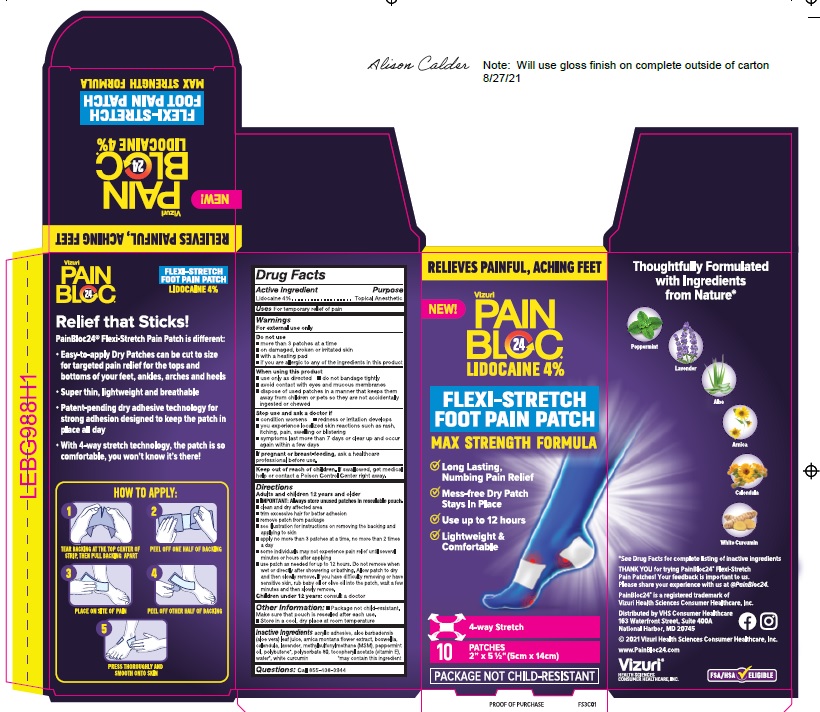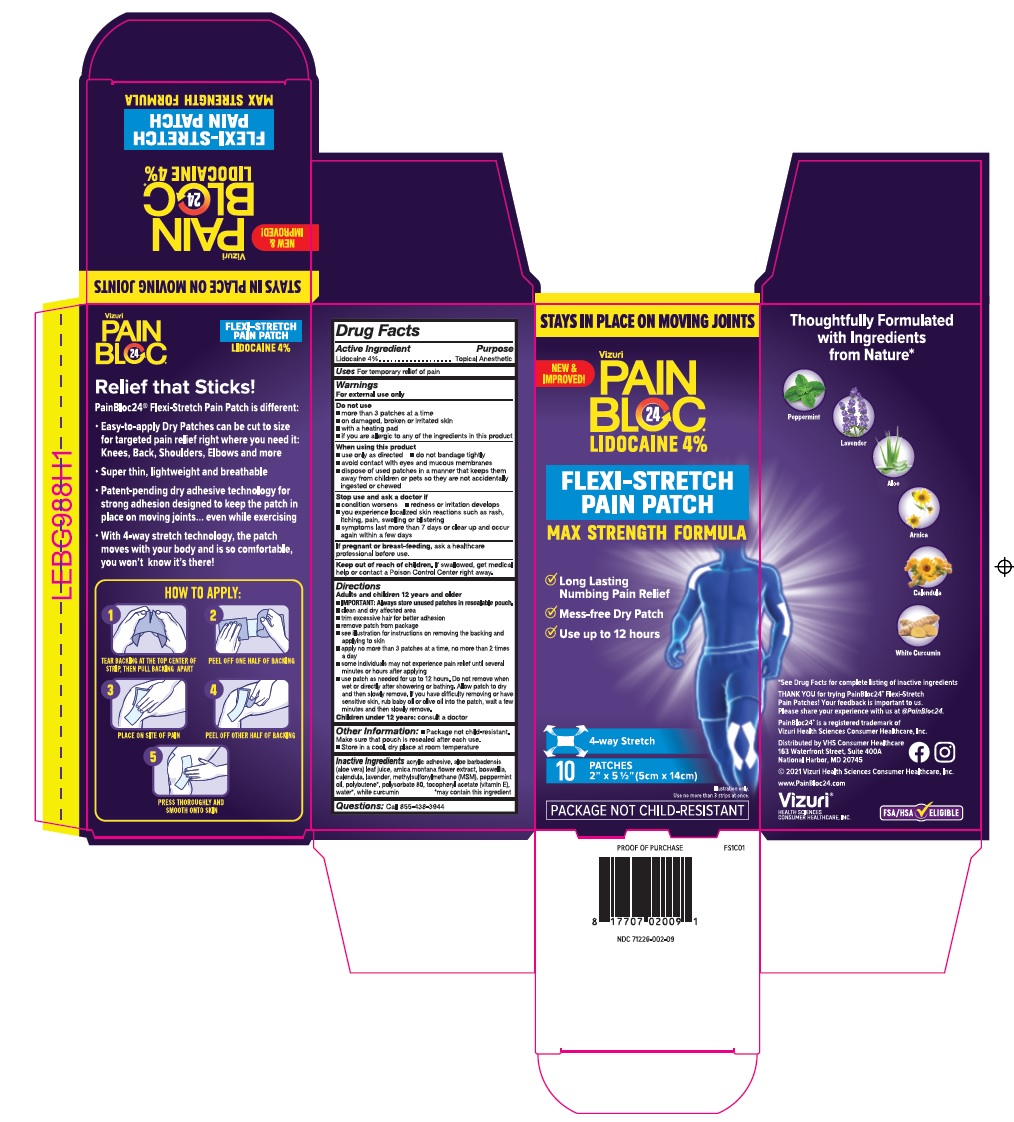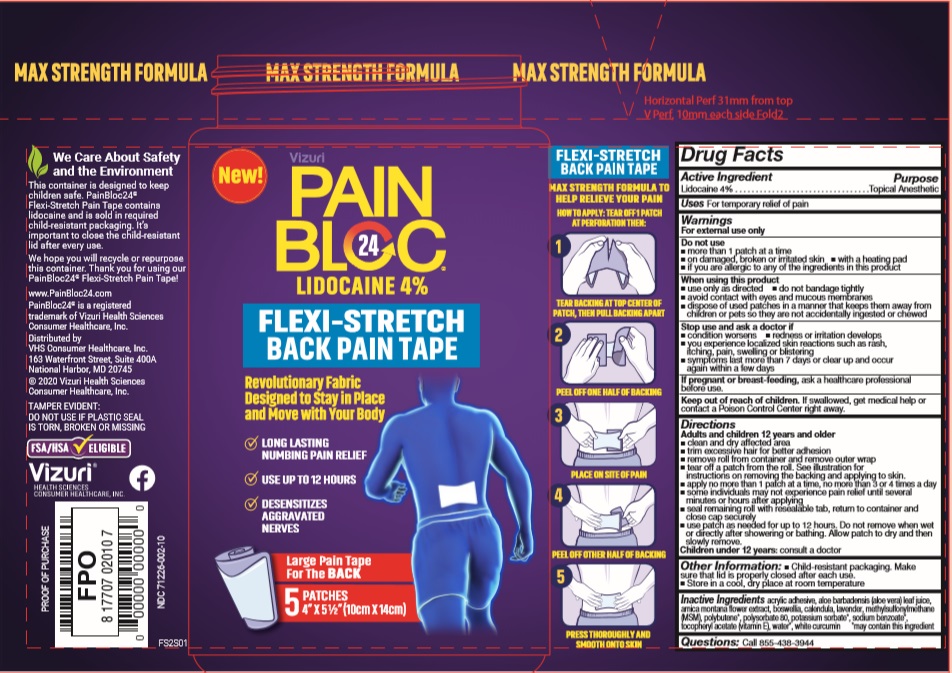 DRUG LABEL: PainBloc24 Flexi-Stretch Pain Tape
NDC: 71226-002 | Form: PATCH
Manufacturer: VIZURI HEALTH SCIENCES LLC
Category: otc | Type: HUMAN OTC DRUG LABEL
Date: 20211001

ACTIVE INGREDIENTS: LIDOCAINE 4 g/1 1
INACTIVE INGREDIENTS: ALOE VERA LEAF; ARNICA MONTANA FLOWER; BOSWELLIA FREREANA WHOLE; CALENDULA ARVENSIS LEAF; LAVANDULA ANGUSTIFOLIA SUBSP. ANGUSTIFOLIA FLOWER; DIMETHYL SULFONE; POLYSORBATE 80; POLYBUTENE (1400 MW); WATER; PEPPERMINT OIL; .ALPHA.-TOCOPHEROL ACETATE; CURCUMIN

PainBloc24 Flexi-Stretch Pain Tape

Active Ingredients

Lidocaine 4%

Purpose

Topical Anesthetic

Uses

For Temporary Relief of Pain.

Warnings

For external use only

Do not use:

- more than 3 strips at a time
- on damaged, broken or irritated skin
- with a heating pad
- if you are allergic to any of the ingredients in this product

When using this product use only as directed:

- do not bandage tightly
- avoid contact with eyes and mucous membranes
- dispose of used strips in a manner that keeps them away from children or pets so they are not accidentally ingested or chewed

Stop use and ask a doctor if:

- condition worsens
- redness or irritation develops
- you experience localized skin reactions such as rash, itching, pain, swelling or blistering
- symptoms last more than 7 days or clear up and occur again within a few days

If pregnant or breast-feeding, ask a healthcare professional before use.

Keep out of reach of children.

If swallowed, get medical help or contact a Poison Control Center right away.

Directions

Adults and Children 12 years and older

- Clean and dry affected area
- Trim excessive hair for better adhesion
- Remove roll from container and remove outer wrap
- Tear off 1 or 2 strips from roll. See illustration for instructions on removing the backing and applying to skin.
- Apply no more than 3 strips at a time, no more than 2 times a day
- Some individuals may not experience pain relief until several minutes or hours after applying
- Seal remaining roll with resealable tab, return to container and close cap securely
- Use strip as needed for up to 12 hours. Do not remove when wet or directly after showering or bathing. Allow strip to dry and then remove.

Children under 12 years: consult a doctor

Inactive Ingredients

aloe barbadensis (aloe vera) leaf juice, arnica montana flower extract, boswellia, calendula, lavender, methylsulfonylmethane (MSM),peppermint oil,polybutene,polysorbate 80,tocopheryl acetate (vitamin E),water,white curcumin